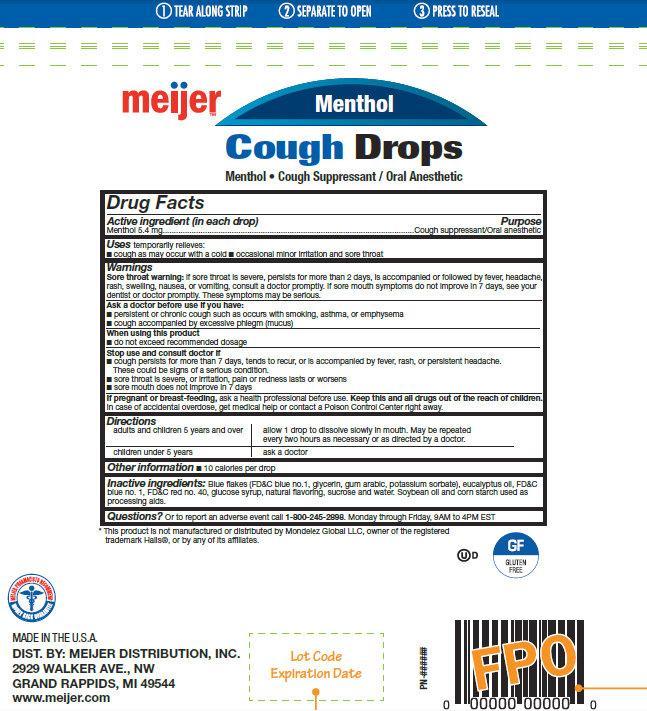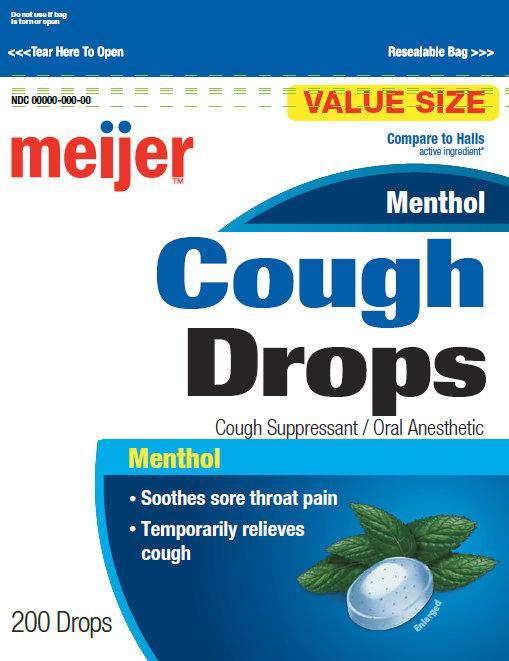 DRUG LABEL: Meijer Menthol Cough Drops
NDC: 41250-078 | Form: LOZENGE
Manufacturer: Meijer Distribution, Inc 
Category: otc | Type: HUMAN OTC DRUG LABEL
Date: 20140506

ACTIVE INGREDIENTS: MENTHOL 5.4 mg/1 1
INACTIVE INGREDIENTS: FD&C BLUE NO. 1; GLYCERIN; ACACIA; POTASSIUM SORBATE; EUCALYPTUS OIL; FD&C RED NO. 40; CORN SYRUP; SUCROSE; WATER; SOYBEAN OIL; STARCH, CORN

Meijer Menthol Cough Drops

Active ingredient (in each drop)

Menthol 5.4 mg

Purpose

Cough suppressant/Oral anesthetic

Uses

temporarily relieves:

- cough as may occur with a cold
- occasional minor irritation and sore throat

Warnings Sore throat warning:

if sore throat is severe, persists for more than 2 days, is accompanied or followed be fever, headache, rash, swelling, nausea, or vomiting, consult a doctor promptly. If sore mouth symptoms do not improve in 7 days, see your dentist or doctor promptly. These symptoms may be serious.

Ask a doctor before use if you have:

- persistent or chronic cough such as occurs with smoking, asthma, or emphysema
- cough accompanied by excessive phlegm (mucus)

When using this product

- do not exceed recommended dosage

Stop use and consult doctor if

- cough persists for more than 7 days, tends to recur, or is accompanied by fever, rash, or persistent headache. These could be signs of a serious condition.
- sore throat is severe, or irritation, pain or redness lasts or worsens
- sore mouth does not improve in 7 days

If pregnant or breast-feeding,

ask a health professional before use.

Keep this and all drugs out of the reach of children.

In case of accidental overdose, get medical help or contact a Poison Control Center right away.

Directions

adults and children 5 years and over | allow 1 drop to dissolve slowly in mouth. May be replaced every two hours as necessary or as directed by a doctor.
children under 5 years | ask a doctor

Other information:

- 10 calories per drop

Inactive ingredients:

Blue fakes (FD&C blue no.1, glycerin, gum arabic, potassium sorbate), eucalyptus oil, FD&C

blue no. 1, FD&C red no. 40, glucose syrup, natural favoring, sucrose and water. Soybean oil and corn starch used as

processing aids.

Questions?

Or to report an adverse event call 1-800-245-2898. Monday - Friday, 9AM to 4PM EST

MADE IN THE U.S.A.

DIST. BY: MEIJER DISTRIBUTION, INC.

2929 WALKER AVE., NW

GRAND RAPPIDS, MI 49544

www.meijer.com

UD GF Gluten-Free

*This product is not manufactured or distributed by Mondelez Global LLC, owner of the registered trademark Halls®, or by any of its afliates.